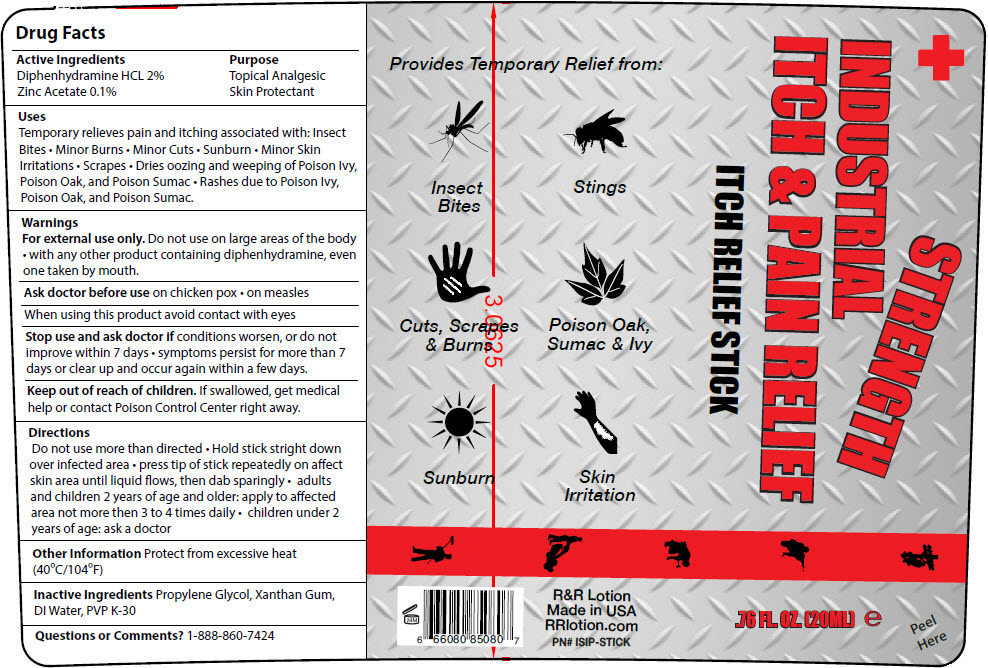 DRUG LABEL: Industrial  Itch and Pain Relief
NDC: 59555-002 | Form: LIQUID
Manufacturer: R & R Lotion, Inc
Category: otc | Type: HUMAN OTC DRUG LABEL
Date: 20250911

ACTIVE INGREDIENTS: DIPHENHYDRAMINE HYDROCHLORIDE 20 mg/1 mL; Zinc Acetate 1 mg/1 mL
INACTIVE INGREDIENTS: water; Xanthan Gum; Propylene Glycol; POVIDONE K30

Industrial Itch and Pain Relief

Drug Facts

ACTIVE INGREDIENT

Active Ingredients | Purpose
Diphenhydramine HCL 2% | Topical Analgesic
Zinc Acetate 0.1% | Skin Protectant

Uses

Temporary relieves pain and itching associated with: Insect Bites

- Minor Burns
- Minor Cuts
- Sunburn
- Minor Skin Irritations
- Scrapes
- Dries oozing and weeping of Poison Ivy, Poison Oak, and Poison Sumac
- Rashes due to Poison Ivy, Poison Oak, and Poison Sumac.

Warnings

DO NOT USE

For external use only. Do not use on large areas of the body

- with any other product containing diphenhydramine, even one taken by mouth.

Ask doctor before use on chicken pox

- on measles

When using this product avoid contact with eyes

Stop use and ask doctor if conditions worsen, or do not improve within 7 days

- symptoms persist for more than 7 days or clear up and occur again within a few days.

Keep out of reach of children. If swallowed, get medical help or contact Poison Control Center right away.

Directions

Do not use more than directed

- Hold stick stright down over infected area
- press tip of stick repeatedly on affect skin area until liquid flows, then dab sparingly
- adults and children 2 years of age and older: apply to affected area not more then 3 to 4 times daily
- children under 2 years of age: ask a doctor

Other Information

Protect from excessive heat (40ºC/104ºF)

Inactive Ingredients

Propylene Glycol, Xanthan Gum, DI Water, PVP K-30

Questions or Comments?

1-888-860-7424

PRINCIPAL DISPLAY PANEL - 20 ML Bottle Label

Provides Temporary Relief from:

Insect
Bites

Stings

Cuts, Scrapes
& Burns

Poison Oak,
Sumac & Ivy

Sunburn

Skin
Irritation

INDUSTRIAL STRENGTH
ITCH & PAIN RELIEF
ITCH RELIEF STICK

R&R Lotion
Made in USA
RRlotion.com
PN# ISIP-STICK

.76 FL. OZ. [20ML] e

Peel
Here